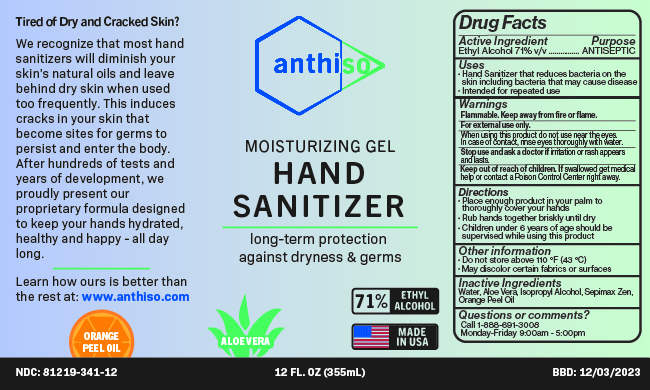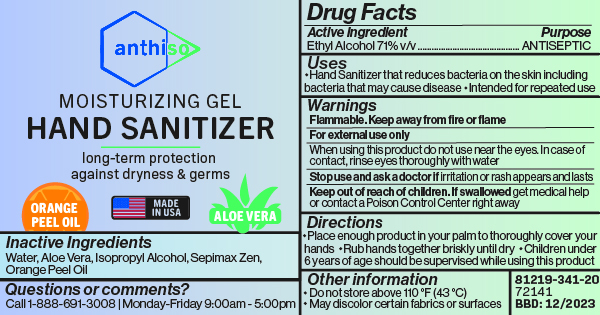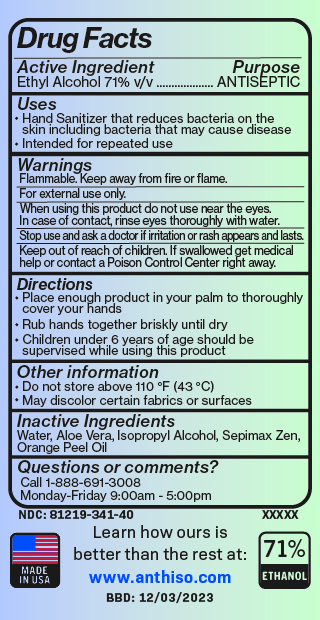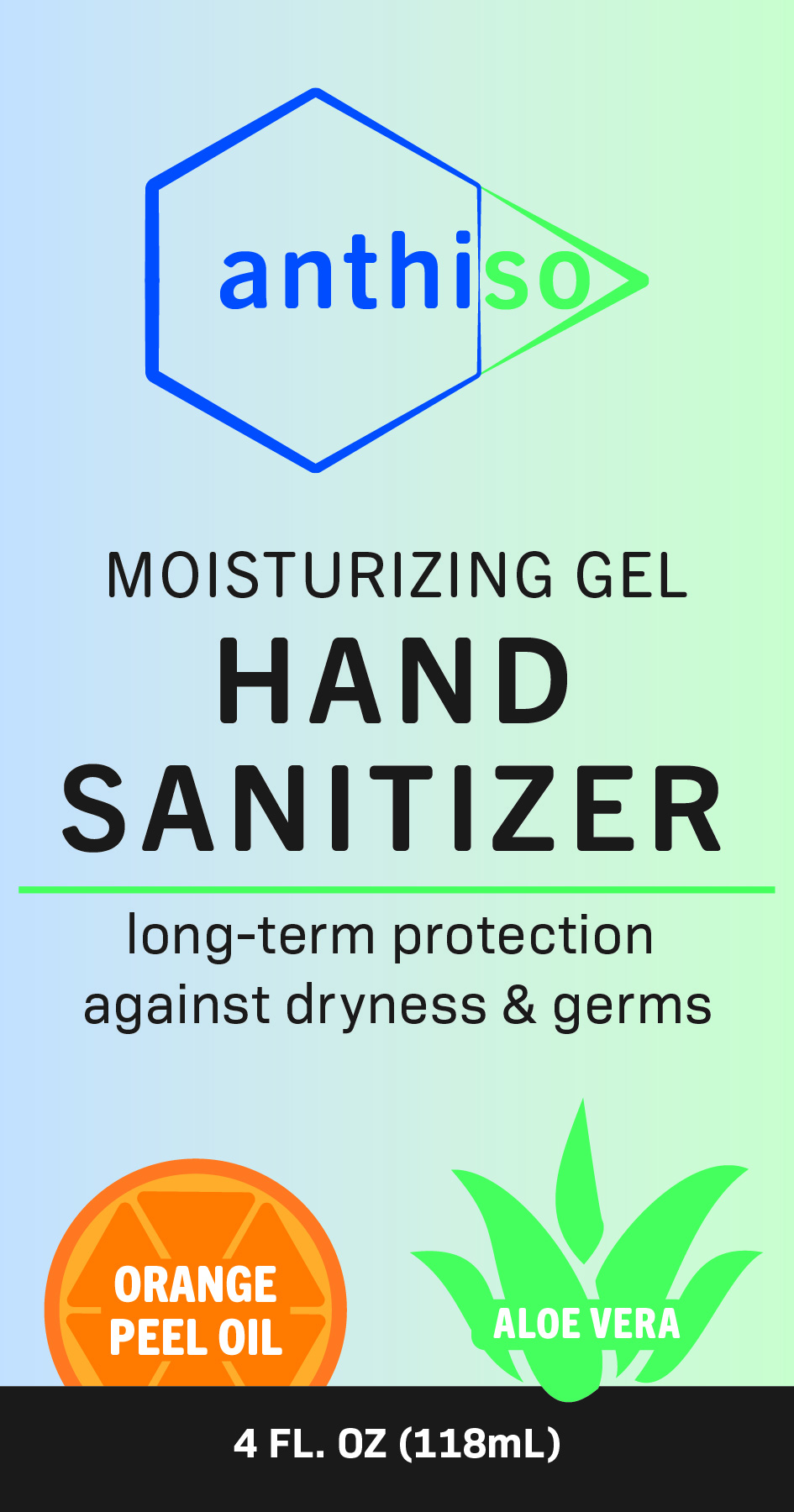 DRUG LABEL: Hand Sanitizer
NDC: 81219-341 | Form: GEL
Manufacturer: Anthiso Inc.
Category: otc | Type: HUMAN OTC DRUG LABEL
Date: 20201202

ACTIVE INGREDIENTS: ALCOHOL 265.2 mL/354.8 mL
INACTIVE INGREDIENTS: ALOE VERA LEAF; WATER; ISOPROPYL ALCOHOL 13.26 mL/354.8 mL; AMMONIUM ACRYLOYLDIMETHYLTAURATE, DIMETHYLACRYLAMIDE, LAURYL METHACRYLATE AND LAURETH-4 METHACRYLATE COPOLYMER, TRIMETHYLOLPROPANE TRIACRYLATE CROSSLINKED (45000 MPA.S)

Anthiso Moisturizing Gel Hand Sanitizer for package sizes: 2oz, 4oz, 8oz, 12oz, 16oz, 1gallon, 5 gallons 55 gallons, 275 gallons.

This is a hand sanitizer manufactured according to 21 CFR part 210, 211, 333, and 330*.* In Health Care Antiseptic Final Rule: Finalizes rulemaking for healthcare antiseptics, a final monograph determination was not made for three active ingredients: Isopropyl alcohol 70-91.3 percent, Benzalkonium chloride, and Alcohol (ethyl alcohol) 60 to 95 percent. These active ingredients were classified as Category III.

Therefore, according to 21 USC 355h, this hand sanitizer is not required to be the subject of an application approved under section 355 of Title 21 because this hand sanitizer is:

(i) classified in category III for safety or effectiveness in the preamble of a proposed rule establishing a tentative final monograph that is the most recently applicable proposal or determination for such drug issued under part 330 of title 21, Code of Federal Regulations;

(ii) in conformity with-

(I) the conditions of use, including indication and dosage strength, if any, described for the Health care personnel hand rub with the active ingredient Alcohol 60 to 95 percent in such preamble or in an applicable subsequent proposed rule;

(II) the proposed requirements for drugs classified in such tentative final monograph in category I in the most recently proposed rule establishing requirements related to such tentative final monograph and in any final rule establishing requirements that are applicable to the drug; and

(III) the general requirements for nonprescription drugs and conditions or requirements under subsection (b) or (k) of 21 USC 355h; and

(iii) in a dosage form that, immediately prior to March 27, 2020, had been used to a material extent and for a material time under section 321(p)(2) of Title 21.

The hand sanitizer is formulated using only the following ingredients:

Alcohol (ethanol) (USP or Food Chemical Codex (FCC) grade) (71%, volume/volume (v/v)) in an aqueous solution denatured with Isopropanol according to Alcohol and Tobacco Tax and Trade Bureau regulations in 27 CFR part 20.
Aloe Vera Leaf.
AMMONIUM ACRYLOYLDIMETHYLTAURATE, DIMETHYLACRYLAMIDE, LAURYL METHACRYLATE AND LAURETH-4 METHACRYLATE COPOLYMER, TRIMETHYLOLPROPANE TRIACRYLATE CROSSLINKED (45000 MPA.S)
Sterile distilled water or boiled cold water.

Active Ingredient

Alcohol 71% v/v

Purpose

ANTISEPTIC

Uses

Hand Sanitizer that reduces bacteria on the skin including bacteria that may cause disease.

Intended for repeated use.

Warnings

Flammable. Keep away from fire or flame.

For external use only.

When using this product do not use near the eyes.

In case of contact, rinse eyes thoroughly with water.

Stop use and ask a doctor if irritation or rash appears and lasts

Keep out of reach of children. If swallowed get medical help or contact a Poison Control Center right away.

Directions

Place enough product in your palm to thoroughly cover your hands

Rub hands together briskly until dry

Children under 6 years of age should be supervised while using this product

Other information

Do not store above 110 °F (43 °C)

May discolor certain fabrics or surfaces

Inactive ingredients

Water, Aloe Vera, Isopropyl Alcohol, Sepimax Zen

Questions or comments?

Call 1-888-691-3008

Monday-Friday 9:00am - 5:00pm

Package Label - Principal Display Panel

These labels are representative of all listed dosage forms: